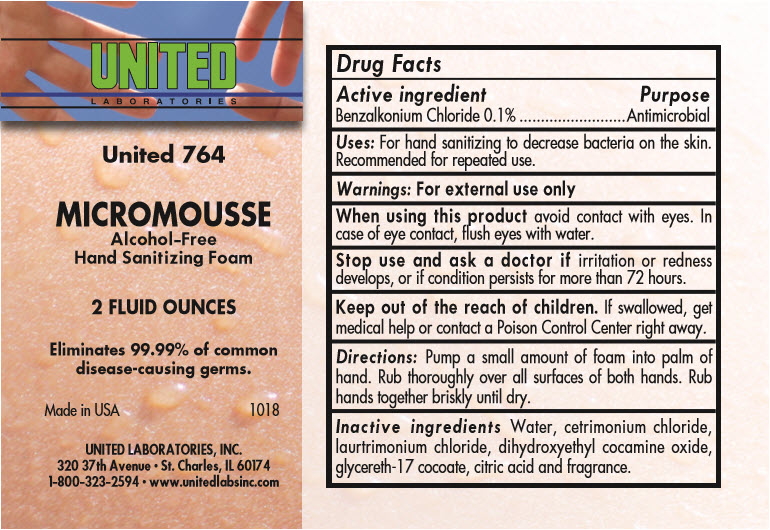 DRUG LABEL: Alcohol-Free Hand Sanitizing Foam
NDC: 63998-764 | Form: SOLUTION
Manufacturer: United Laboratories Inc.
Category: otc | Type: HUMAN OTC DRUG LABEL
Date: 20241125

ACTIVE INGREDIENTS: BENZALKONIUM CHLORIDE 1 mg/1 mL
INACTIVE INGREDIENTS: WATER; CETRIMONIUM CHLORIDE; LAURTRIMONIUM CHLORIDE; DIHYDROXYETHYL COCAMINE OXIDE; GLYCERETH-17 COCOATE; CITRIC ACID MONOHYDRATE

Alcohol-Free Hand Sanitizing Foam 63998-764

Drug Facts

Active ingredient

Benzalkonium Chloride 0.1%

Purpose

Antimicrobial

Uses

For hand sanitizing to decrease bacteria on the skin. Recommended for repeated use.

Warnings

For external use only

WHEN USING

When using this productavoid contact with eyes. In case of eye contact, flush eyes with water.

Stop use and ask a doctor ifirritation or redness develops, or if condition persists for more than 72 hours.

KEEP OUT OF REACH OF CHILDREN

Keep out of the reach of children.If swallowed, get medical help or contact a Poison Control Center right away.

Directions

Pump a small amount of foam into palm of hand. Rub thoroughly over all surfaces of both hands. Rub hands together briskly until dry.

Inactive ingredients

Water, cetrimonium chloride, laurtrimonium chloride, dihydroxyethyl cocamine oxide, glycereth-17 cocoate, citric acid and fragrance.

PRINCIPAL DISPLAY PANEL - 2 Ounce Bottle Label

UNITED
LABORATORIES

United 764

MICROMOUSSE

Alcohol-Free
Hand Sanitizing Foam

2 FLUID OUNCES

Eliminates 99.99% of common
disease-causing germs.

Made in USA
1018

UNITED LABORATORIES, INC.
320 37th Avenue • St. Charles, IL 60174
1-800-323-2594 • www.unitedlabsinc.com